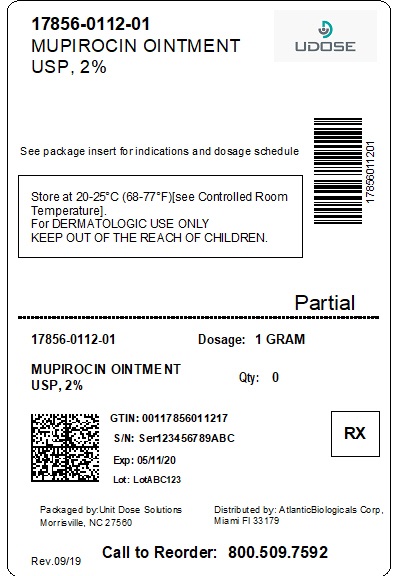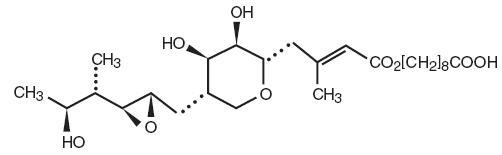 DRUG LABEL: mupirocin
NDC: 17856-0112 | Form: OINTMENT
Manufacturer: ATLANTIC BIOLOGICALS CORP.
Category: prescription | Type: HUMAN PRESCRIPTION DRUG LABEL
Date: 20250528

ACTIVE INGREDIENTS: MUPIROCIN 20 mg/1 g
INACTIVE INGREDIENTS: POLYETHYLENE GLYCOL, UNSPECIFIED

MUPIROCIN OINTMENT USP, 2%

For Dermatologic Use

Rx Only

DESCRIPTION

Each gram of Mupirocin Ointment USP, 2% contains 20 mg mupirocin in a bland water miscible ointment base (polyethylene glycol ointment, NF) consisting of polyethylene glycol 400 and polyethylene glycol 3350. Mupirocin is a naturally occurring antibiotic. The chemical name is ()-(2 ,3 ,4 ,5)-5-[(2 ,3 ,4 ,5)-2,3-Epoxy-5-hydroxy-4-methylhexyl]tetrahydro-3,4-dihydroxy-β-methyl-2 -pyran-2-crotonic acid, ester with 9-hydroxynonanoic acid. The molecular formula of mupirocin is C H O and the molecular weight is 500.62. ESRRSSSSSH26449

The chemical structure is:

CLINICAL PHARMACOLOGY

Application of C-labeled mupirocin ointment to the lower arm of normal male subjects followed by occlusion for 24 hours showed no measurable systemic absorption (<1.1 nanogram mupirocin per milliliter of whole blood). Measurable radioactivity was present in the stratum corneum of these subjects 72 hours after application.^14

Following intravenous or oral administration, mupirocin is rapidly metabolized. The principal metabolite, monic acid, is eliminated by renal excretion, and demonstrates no antibacterial activity. In a trial conducted in 7 healthy adult male subjects, the elimination half-life after intravenous administration of mupirocin was 20 to 40 minutes for mupirocin and 30 to 80 minutes for monic acid. The pharmacokinetics of mupirocin has not been studied in individuals with renal insufficiency.

Microbiology -

Mupirocin is an antibacterial agent produced by fermentation using the organism . Mupirocin inhibits bacterial protein synthesis by reversibly and specifically binding to bacterial isoleucyl transfer-RNA (tRNA) synthetase. Due to this unique mode of action, mupirocin does not demonstrate cross-resistance with other classes of antimicrobial agents. Pseudomonasfluorescens

When mupirocin resistance occurs, it results from the production of a modified isoleucyl-tRNA synthetase, or the acquisition of, by genetic transfer, a plasmid mediating a new isoleucyl-tRNA synthetase. High-level plasmid-mediated resistance (MIC >512 mcg/mL) has been reported in increasing numbers of isolates of and with higher frequency in coagulase-negative staphylococci. Mupirocin resistance occurs with greater frequency in methicillin-resistant than methicillin-susceptible staphylococci. Because of the occurrence of mupirocin resistance in methicillin-resistant (MRSA), it is appropriate to test MRSA populations for mupirocin susceptibility prior to the use of mupirocin using a standardized method. Staphylococcus aureus Staphylococcusaureu^1,2,3

Mupirocin is bactericidal at concentrations achieved by topical administration. Mupirocin is highly protein-bound (>97%), and the effect of wound secretions on the MICs of mupirocin has not been determined.

Mupirocin has been shown to be active against susceptible strains of , both and in clinical trials (see INDICATIONS AND USAGE). The following data are available, . Mupirocin is active against most isolates of . S. aureus and Streptococcus pyogenesin vitroin vitrobut their clinical significance is unknown Staphylococcus epidermidis

INDICATIONS AND USAGE

Mupirocin Ointment USP, 2% is indicated for the topical treatment of impetigo due to: and . S. aureus S. pyogenes

CONTRAINDICATIONS

This drug is contraindicated in patients with known hypersensitivity to any of the constituents of the product.

WARNINGS

Avoid contact with the eyes. In case of accidental contact, rinse well with water.

In the event of sensitization or severe local irritation from Mupirocin Ointment USP, 2%, usage should be discontinued.

- associated diarrhea (CDAD) has been reported with use of nearly all antibacterial agents, including mupirocin, and may range in severity from mild diarrhea to fatal colitis. Treatment with antibacterial agents alters the normal flora of the colon leading to overgrowth of . Clostridium difficile C. difficile

produces toxins A and B which contribute to the development of CDAD. Hypertoxin-producing isolates of cause increased morbidity and mortality, as these infections can be refractory to antimicrobial therapy and may require colectomy. CDAD must be considered in all patients who present with diarrhea following antibacterial drug use. Careful medical history is necessary since CDAD has been reported to occur over two months after the administration of antibacterial agents. C. difficile C. difficile

If CDAD is suspected or confirmed, ongoing antibacterial drug use not directed against may need to be discontinued. Appropriate fluid and electrolyte management, protein supplementation, antibacterial treatment of , and surgical evaluation should be instituted as clinically indicated. C. difficile C. difficile

PRECAUTIONS

As with other antibacterial products, prolonged use may result in overgrowth of nonsusceptible organisms, including fungi.

Mupirocin Ointment USP, 2% is not formulated for use on mucosal surfaces. Intranasal use has been associated with isolated reports of stinging and drying.

A paraffin-based formulation - *Bactroban Nasal® (mupirocin calcium ointment) - is available for intranasal use.

Polyethylene glycol can be absorbed from open wounds and damaged skin and is excreted by the kidneys. In common with other polyethylene glycol-based ointments, Mupirocin Ointment USP, 2% should not be used in conditions where absorption of large quantities of polyethylene glycol is possible, especially if there is evidence of moderate or severe renal impairment.

Mupirocin Ointment USP, 2% should not be used with intravenous cannulae or at central intravenous sites because of the potential to promote fungal infections and antimicrobial resistance.

Information for Patients -

Use this medication only as directed by the healthcare provider. It is for external use only. Avoid contact with the eyes. If Mupirocin Ointment USP, 2% gets in or near the eyes, rinse thoroughly with water. The medication should be stopped and the healthcare provider contacted if irritation, severe itching, or rash occurs. If impetigo has not improved in 3 to 5 days, contact the healthcare provider.

- Drug Interactions

The effect of the concurrent application of Mupirocin Ointment USP, 2% and other drug products has not been studied.

Carcinogenesis, Mutagenesis, Impairment of Fertility -

Long-term studies in animals to evaluate carcinogenic potential of mupirocin have not been conducted.

Results of the following studies performed with mupirocin calcium or mupirocin sodium and did not indicate a potential for genotoxicity: Rat primary hepatocyte unscheduled DNA synthesis, sediment analysis for DNA strand breaks, reversion test (Ames), mutation assay, metaphase analysis of human lymphocytes, mouse lymphoma assay, and bone marrow micronuclei assay in mice. in vitroin vivo Salmonella Escherichia coli

Reproduction studies were performed in male and female rats with mupirocin administered subcutaneously at doses up to 14 times a human topical dose (approximately 60 mg mupirocin per day) on a mg/m basis and revealed no evidence of impaired fertility and reproductive performance from mupirocin.^2

Pregnancy:

Teratogenic Effects:

Pregnancy Category B -

Reproduction studies have been performed in rats and rabbits with mupirocin administered subcutaneously at doses up to 22 and 43 times, respectively, the human topical dose (approximately 60 mg mupirocin per day) on a mg/m basis and revealed no evidence of harm to the fetus due to mupirocin. There are, however, no adequate and well-controlled studies in pregnant women. Because animal studies are not always predictive of human response, this drug should be used during pregnancy only if clearly needed.^2

Nursing Mothers -

It is not known whether this drug is excreted in human milk. Because many drugs are excreted in human milk, caution should be exercised when Mupirocin Ointment USP, 2% is administered to a nursing woman.

Pediatric Use -

The safety and effectiveness of Mupirocin Ointment USP, 2% have been established in the age range of 2 months to 16 years. Use of mupirocin ointment USP, 2% in these age groups is supported by evidence from adequate and well-controlled trials of mupirocin ointment USP, 2% in impetigo in pediatric subjects studied as part of the pivotal clinical trials (see). CLINICAL STUDIES

ADVERSE REACTIONS

The following local adverse reactions have been reported in connection with the use of mupirocin ointment USP, 2%: burning, stinging, or pain in 1.5% of subjects; itching in 1% of subjects; rash, nausea, erythema, dry skin, tenderness, swelling, contact dermatitis, and increased exudate in less than 1% of subjects. Systemic allergic reactions, including anaphylaxis, urticaria, angioedema and generalized rash have been reported in patients treated with mupirocin formulations.

DOSAGE AND ADMINISTRATION

A small amount of Mupirocin Ointment USP, 2% should be applied to the affected area 3 times daily. The area treated may be covered with a gauze dressing if desired. Patients not showing a clinical response within 3 to 5 days should be re-evaluated.

CLINICAL STUDIES

The efficacy of topical mupirocin ointment USP, 2% in impetigo was tested in 2 trials. In the first, subjects with impetigo were randomized to receive either mupirocin ointment USP, 2% or vehicle placebo 3 times daily for 8 to 12 days. Clinical efficacy rates at end of therapy in the evaluable populations (adults and pediatric subjects included) were 71% for mupirocin ointment USP, 2% (n=49) and 35% for vehicle placebo (n=51). Pathogen eradication rates in the evaluable populations were 94% for mupirocin ointment USP, 2% and 62% for vehicle placebo. There were no side effects reported in the group receiving mupirocin ointment USP, 2%. In the second trial, subjects with impetigo were randomized to receive either mupirocin ointment USP, 2% 3 times daily or 30 to 40 mg/kg oral erythromycin ethylsuccinate per day (this was an unblinded trial) for 8 days. There was a follow-up visit 1 week after treatment ended. Clinical efficacy rates at the follow-up visit in the evaluable populations (adults and pediatric subjects included) were 93% for mupirocin ointment USP, 2% (n=29) and 78.5% for erythromycin (n=28). Pathogen eradication rates in the evaluable populations were 100% for both test groups. There were no side effects reported in the group receiving mupirocin ointment USP, 2%.

Pediatrics -

There were 91 pediatric subjects aged 2 months to 15 years in the first trial described above. Clinical efficacy rates at end of therapy in the evaluable populations were 78% for mupirocin ointment USP, 2% (n=42) and 36% for vehicle placebo (n=49). In the second trial described above, all subjects were pediatric except 2 adults in the group receiving mupirocin ointment USP, 2%. The age range of the pediatric subjects was 7 months to 13 years. The clinical efficacy rate for mupirocin ointment USP, 2% (n=27) was 96%, and for erythromycin it was unchanged (78.5%).

HOW SUPPLIED

NDC:17856-0112-1 in a SYRINGE of 1 OINTMENTS

REFERENCES

1. Clinical and Laboratory Standards Institute (CLSI). Methods for Dilution Antimicrobial Susceptibility Tests for Bacteria that Grow Aerobically; Approved Standard -Tenth Edition. CLSI document M07-A10 [2015], Clinical and Laboratory Standards Institute, 950 West Valley Road, Suite 2500, Wayne, Pennsylvania 19087, USA.

2. Clinical and Laboratory Standards Institute (CLSI). Performance Standards for Antimicrobial Disk Diffusion Susceptibility Tests; Approved Standard – Twelfth Edition. CLSI document M02-A12 [2015], Clinical and Laboratory Standards Institute, 950 West Valley Road, Suite 2500, Wayne, Pennsylvania 19087, USA.

3. Finlay JE, Miller LA, Poupard JA. Interpretive criteria for testing susceptibility of staphylococci to mupirocin. 1997;41(5):1137-1139. Antimicrob Agents Chemother

Made in Israel

Manufactured By Perrigo

Yeruham 80500, Israel

Distributed By

Perrigo®

Allegan, MI 49010 • www.perrigo.com

Rev 05-15

1N200 RC J6

DISTRIBUTED BY:

ATLANTIC BIOLOGICALS CORP.

MIAMI, FL 33179